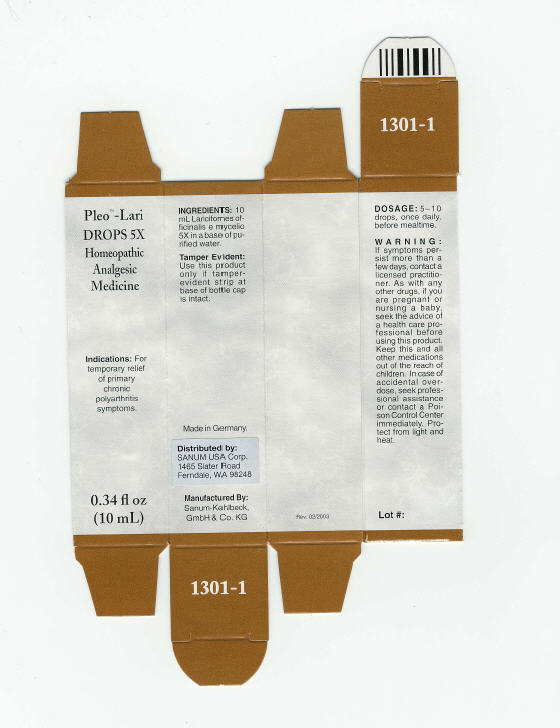 DRUG LABEL: Pleo Lari
NDC: 60681-1301 | Form: SOLUTION/ DROPS
Manufacturer: Sanum Kehlbeck GmbH & Co. KG
Category: homeopathic | Type: HUMAN OTC DRUG LABEL
Date: 20110801

ACTIVE INGREDIENTS: laricifomes officinalis fruiting body 5 [hp_X]/10 mL
INACTIVE INGREDIENTS: water

Pleo™ –Lari
DROPS 5X

Homeopathic Analgesic Medicine

0.34 fl oz
(10 mL)

Indications

PURPOSE

For temporary relief of primary chronic polyarthritis symptoms.

INGREDIENTS

10 mL Laricifomes officinalis e mycelio 5X.

INACTIVE INGREDIENT

Purified Water

Tamper Evident

Use this product only if tamper-evident strip at base of bottle cap is intact.

DOSAGE

5–10 drops, once daily, before mealtime.

WARNING

If symptoms persist more than a few days, contact a licensed practitioner. As with any other drugs, if you are pregnant or nursing a baby, seek the advice of a health care professional before using this product.

KEEP OUT OF REACH OF CHILDREN

Keep this and all other medications out of the reach of children. In case of accidental overdose, seek professional assistance or contact a Poison Control Center immediately.

STORAGE AND HANDLING

Protect from light and heat.

Made in Germany.

Distributed by:
SANUM USA Corp.
1465 Slater Road
Ferndale, WA 98248

Manufactured By:
Sanum-Kehlbeck,
GmbH & Co. KG

Rev. 02/2003

PRINCIPAL DISPLAY PANEL - 10 mL Bottle Carton

Pleo™ –Lari
DROPS 5X
Homeopathic
Analgesic
Medicine

Indications: For
temporary relief
of primary
chronic
polyarthritis
symptoms.

0.34 fl oz
(10 mL)